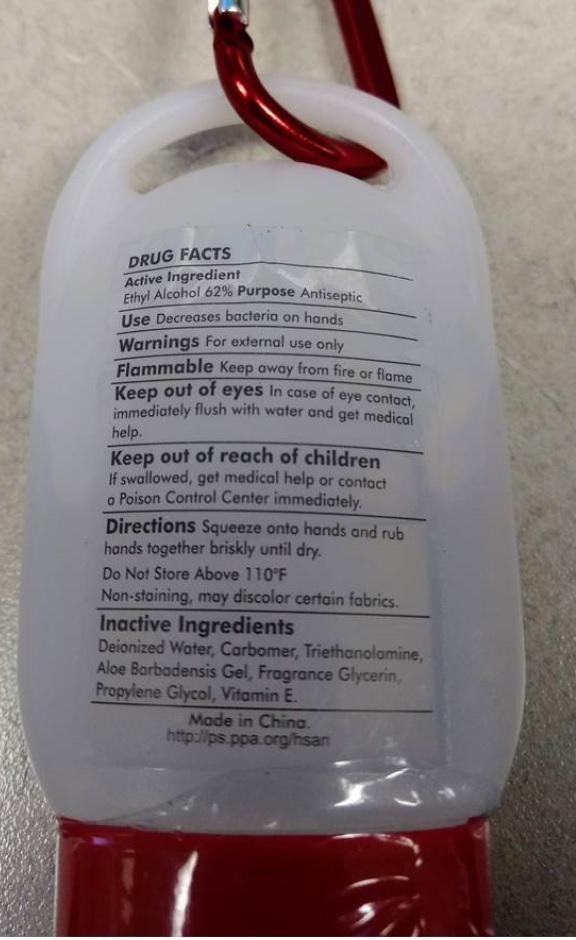 DRUG LABEL: Hand Sanitizer
NDC: 73752-319 | Form: GEL
Manufacturer: Specialty Graphics
Category: otc | Type: HUMAN OTC DRUG LABEL
Date: 20221027

ACTIVE INGREDIENTS: ALCOHOL 62 mL/100 mL
INACTIVE INGREDIENTS: WATER; CARBOMER HOMOPOLYMER, UNSPECIFIED TYPE; TROLAMINE; ALOE VERA LEAF; GLYCERIN; PROPYLENE GLYCOL; .ALPHA.-TOCOPHEROL

Hand Sanitizer

Active Ingredient

Ethyl Alcohol 62%

Purpose

Antiseptic

INDICATIONS AND USAGE

Use Decreases bacteria on hands

Warnings For external use only

Flammable Keep away from fire or flame

Keep out of eyes In case of eye contact, immediately flush with water and get medical help.

Keep out of reach of children

If swallowed, get medical help or contact a Poison Control Center immediately.

DOSAGE AND ADMINISTRATION

Directions Squeeze onto hands and rub hands together briskly until dry.

Do Not Store Above 110°F

Non-staining, may discolor certain fabrics.

Inactive Ingredients

Deionized Water, Carbomer, Triethanolamine, Aloe Barbadensis Gel, Fragrance Glycerin, Propylene Glycol, Vitamin E.

Made in China.

http://ps.ppa.org/hsan